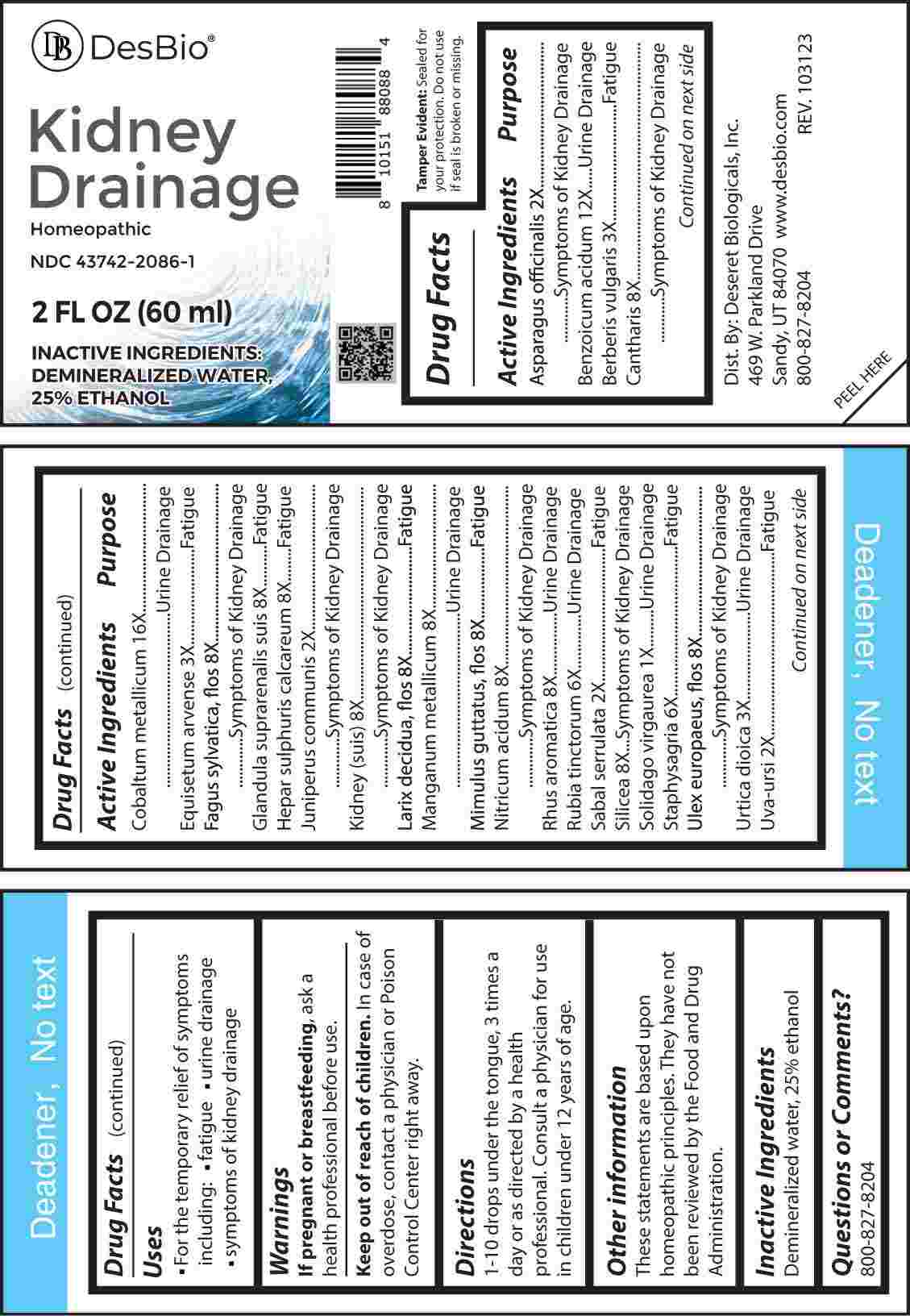 DRUG LABEL: Kidney Drainage
NDC: 43742-2086 | Form: LIQUID
Manufacturer: Deseret Biologicals, Inc.
Category: homeopathic | Type: HUMAN OTC DRUG LABEL
Date: 20240220

ACTIVE INGREDIENTS: SOLIDAGO VIRGAUREA FLOWERING TOP 1 [hp_X]/1 mL; ASPARAGUS 2 [hp_X]/1 mL; JUNIPER BERRY 2 [hp_X]/1 mL; SAW PALMETTO 2 [hp_X]/1 mL; ARCTOSTAPHYLOS UVA-URSI LEAF 2 [hp_X]/1 mL; BERBERIS VULGARIS ROOT BARK 3 [hp_X]/1 mL; EQUISETUM ARVENSE TOP 3 [hp_X]/1 mL; URTICA DIOICA WHOLE 3 [hp_X]/1 mL; RUBIA TINCTORUM ROOT 6 [hp_X]/1 mL; DELPHINIUM STAPHISAGRIA SEED 6 [hp_X]/1 mL; LYTTA VESICATORIA 8 [hp_X]/1 mL; FAGUS SYLVATICA FLOWERING TOP 8 [hp_X]/1 mL; SUS SCROFA ADRENAL GLAND 8 [hp_X]/1 mL; CALCIUM SULFIDE 8 [hp_X]/1 mL; PORK KIDNEY 8 [hp_X]/1 mL; LARIX DECIDUA FLOWERING TOP 8 [hp_X]/1 mL; MANGANESE 8 [hp_X]/1 mL; MIMULUS GUTTATUS FLOWERING TOP 8 [hp_X]/1 mL; NITRIC ACID 8 [hp_X]/1 mL; RHUS AROMATICA ROOT BARK 8 [hp_X]/1 mL; SILICON DIOXIDE 8 [hp_X]/1 mL; ULEX EUROPAEUS FLOWER 8 [hp_X]/1 mL; BENZOIC ACID 12 [hp_X]/1 mL; COBALT 16 [hp_X]/1 mL
INACTIVE INGREDIENTS: WATER; ALCOHOL

DRUG FACTS:

ACTIVE INGREDIENTS:

Asparagus Officinalis 2X, Benzoicum Acidum 12X, Berberis Vulgaris 3X, Cantharis 8X, Cobaltum Metallicum 16X, Equisetum Arvense 3X, Fagus Sylvatica, Flos 8X, Glandula Suprarenalis Suis 8X, Hepar Sulphuris Calcareum 8X, Juniperus Communis 2X, Kidney (Suis) 8X, Larix Decidua, Flos 8X, Manganum Metallicum 8X, Mimulus Guttatus, Flos 8X, Nitricum Acidum 8X, Rhus Aromatica 8X, Rubia Tinctorum 6X, Sabal Serrulata 2X, Silicea 8X, Solidago Virgaurea 1X, Staphysagria 6X, Ulex Europaeus, Flos 8X, Urtica Dioica 3X, Uva-Ursi 2X.

PURPOSE:

Asparagus Officinalis – Symptoms of Kidney Drainage, Benzoicum Acidum – Urine Drainage, Berberis Vulgaris - Fatigue, Cantharis – Symptoms of Kidney Drainage, Cobaltum Metallicum – Urine Drainage, Equisetum Arvense - Fatigue, Fagus Sylvatica, Flos – Symptoms of Kidney Drainage, Glandula Suprarenalis Suis - Fatigue, Hepar Sulphuris Calcareum - Fatigue, Juniperus Communis – Symptoms of Kidney Drainage, Kidney (Suis) - Symptoms of Kidney Drainage, Larix Decidua, Flos - Fatigue, Manganum Metallicum – Urine Drainage, Mimulus Guttatus, Flos - Fatigue, Nitricum Acidum - Symptoms of Kidney Drainage, Rhus Aromatica – Urine Drainage, Rubia Tinctorum – Urine Drainage, Sabal Serrulata - Fatigue, Silicea - Symptoms of Kidney Drainage, Solidago Virgaurea – Urine Drainage, Staphysagria - Fatigue, Ulex Europaeus, Flos - Symptoms of Kidney Drainage, Urtica Dioica – Urine Drainage, Uva-Ursi - Fatigue

USES:

• For the temporary relief of symptoms including:

• fatigue • urine drainage • symptoms of kidney drainage

These statements are based upon homeopathic principles. They have not been reviewed by the Food and Drug Administration.

WARNINGS:

If pregnant or breast-feeding, ask a health professional before use.

Keep out of reach of children. In case of overdose, contact a physician or Poison Control Center right away.

Tamper Evident: Sealed for your protection. Do not use if seal is broken or missing.

KEEP OUT OF REACH OF CHILDREN:

In case of overdose, contact a physician or Poison Control Center right away.

DIRECTIONS:

1-10 drops under the tongue, 3 times a day or as directed by a health professional. Consult a physician for use in children under 12 years of age.

INACTIVE INGREDIENTS:

Demineralized water, 25% ethanol

QUESTIONS:

Dist. By: Deseret Biologicals, Inc.

469 W. Parkland Drive

Sandy, UT 84070

www.desbio.com

800-827-8204

PACKAGE DISPLAY LABEL:

Des Bio

Kidney

Drainage

Homeopathic

NDC 43742-2086-1

2 FL OZ (60 ml)